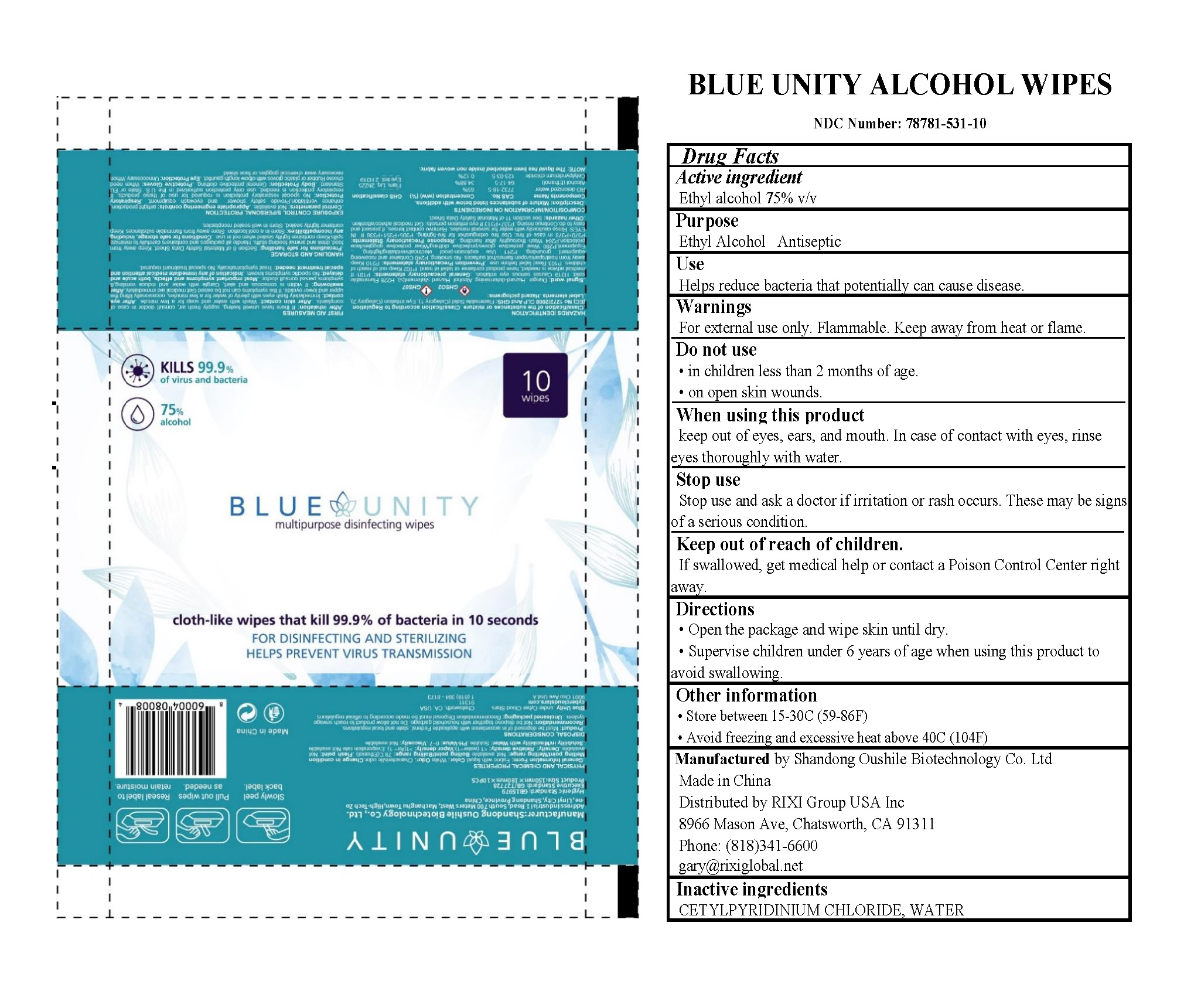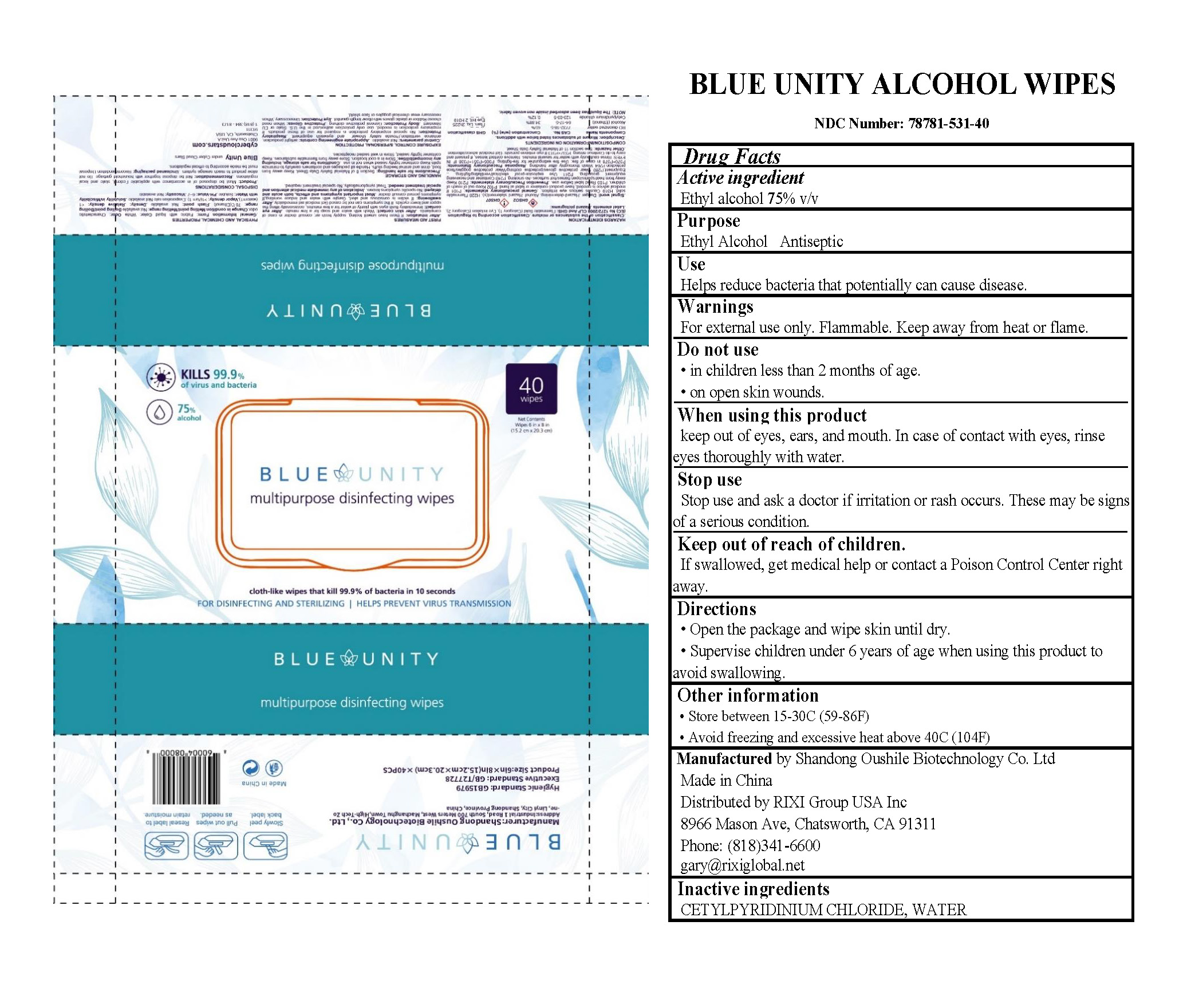 DRUG LABEL: Blue Unity Alcohol Wipes
NDC: 78781-531 | Form: CLOTH
Manufacturer: Shandong Oushile Biotechnology Co.Ltd
Category: otc | Type: HUMAN OTC DRUG LABEL
Date: 20201019

ACTIVE INGREDIENTS: ALCOHOL 75 mL/100 1
INACTIVE INGREDIENTS: CETYLPYRIDINIUM CHLORIDE; WATER

Shandong Oushile Biotechnology Co.Ltd

Active Ingredient

Ethyl Alcohol 75% v/v

Purpose

Ethyl Alcohol Antiseptic

Use

Helps reduce bacteria that potentially can cause disease.

Warnings

For external use only. Flammable. Keep away from heat or flame.

Do not use

- in children less than 2 months of age.
- on open skin wounds.

When using this product

keep out of eyes, ears, and mouth. In case of contact with eyes, rinse eyes thoroughly with water.

Stop use

Stop use and ask a doctor if irritation or rash occurs. These may be signs of a serious condition.

Keep out of reach of children.

If swallowed, get medical help or contact a Poison Control Center right away.

Directions

- Open the package and wipe skin until dry.
- Supervise children under 6 years of age when using this product to avoid swallowing.

Other information

- Store between 15-30C (59-86F)
- Avoid freezing and excessive heat above 40C (104F)

Manufactured by Shandong Oushile Biotechnology Co.Ltd

Made in China

Distributed by RIXI Group USA Inc
8966 Mason Ave, Chatsworth, CA 91311
Phone: (818)341-6600
gary@rixiglobal.net

Inactive ingredients

CETYLPYRIDINIUM CHLORIDE, WATER